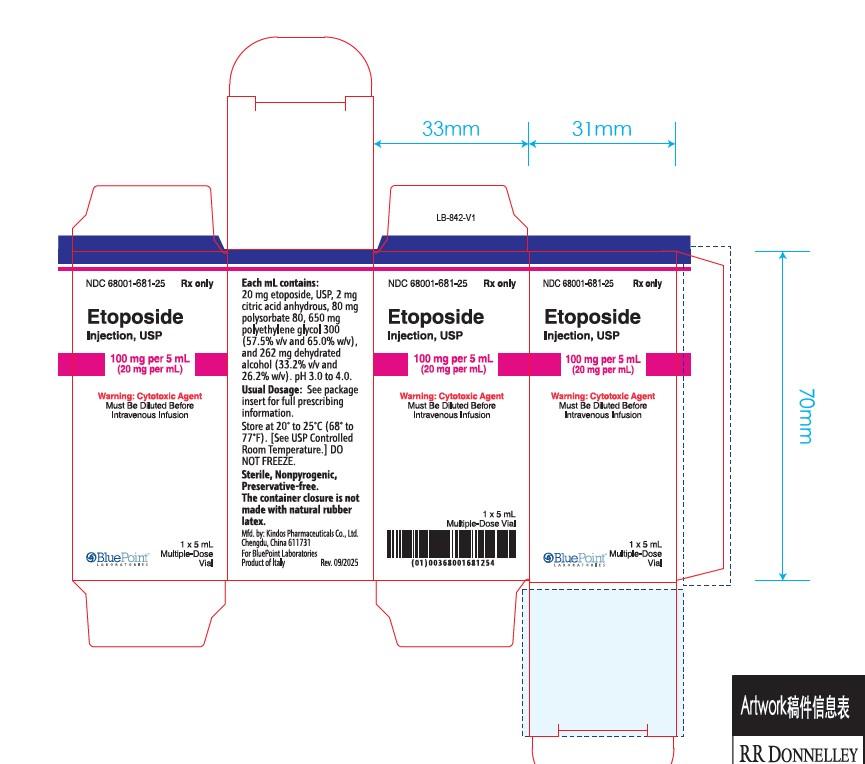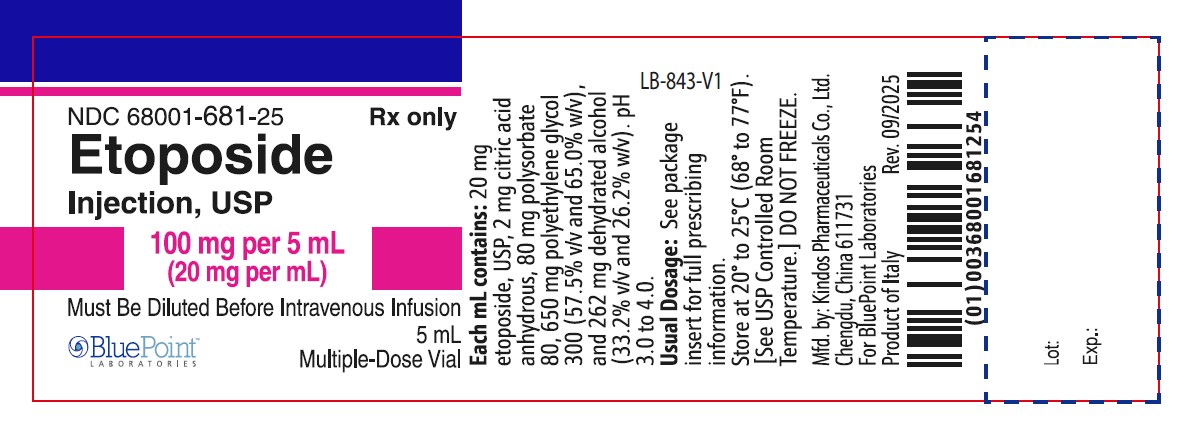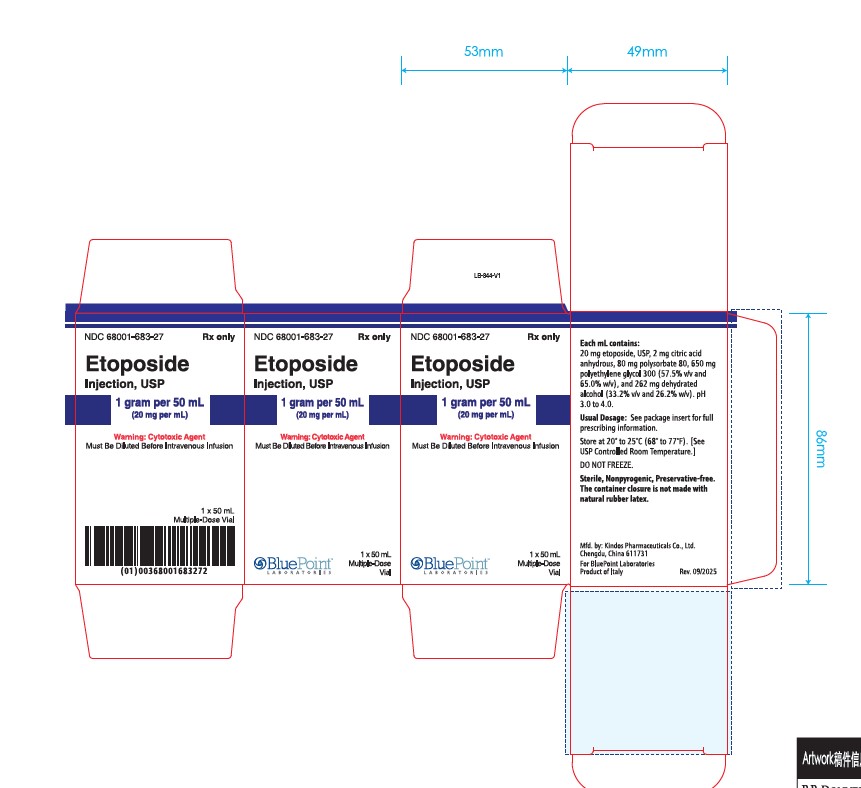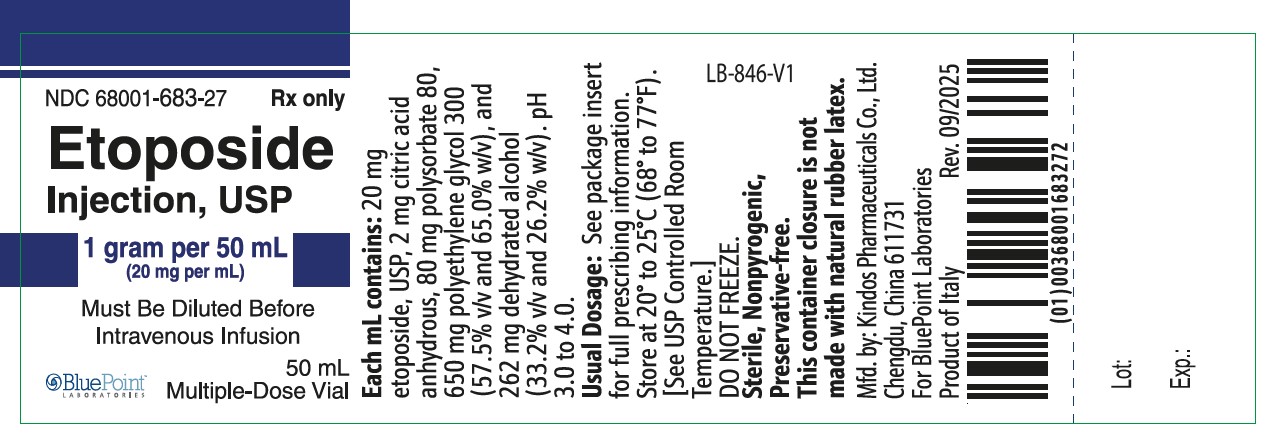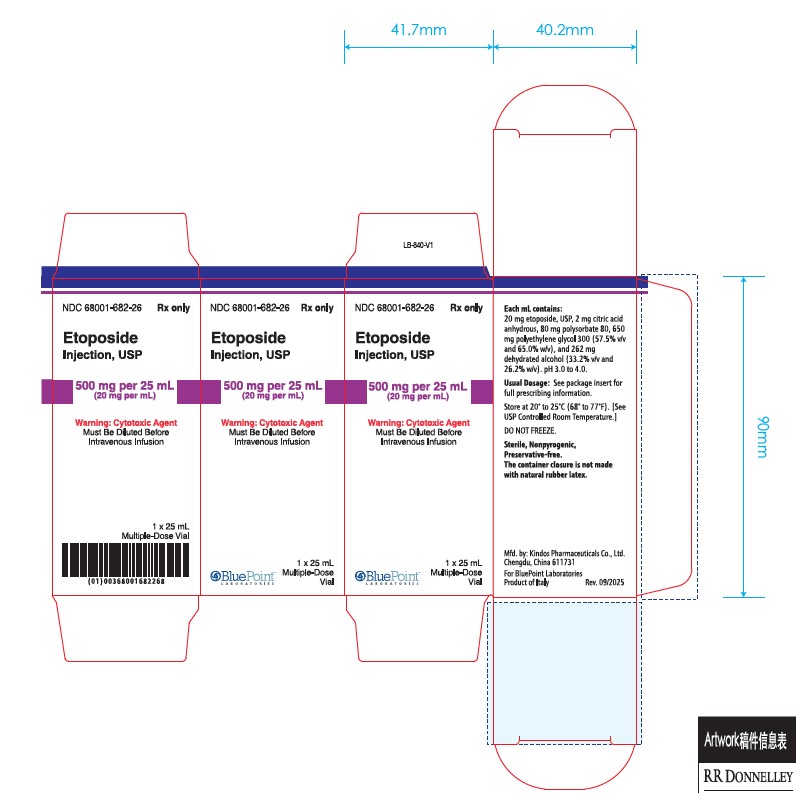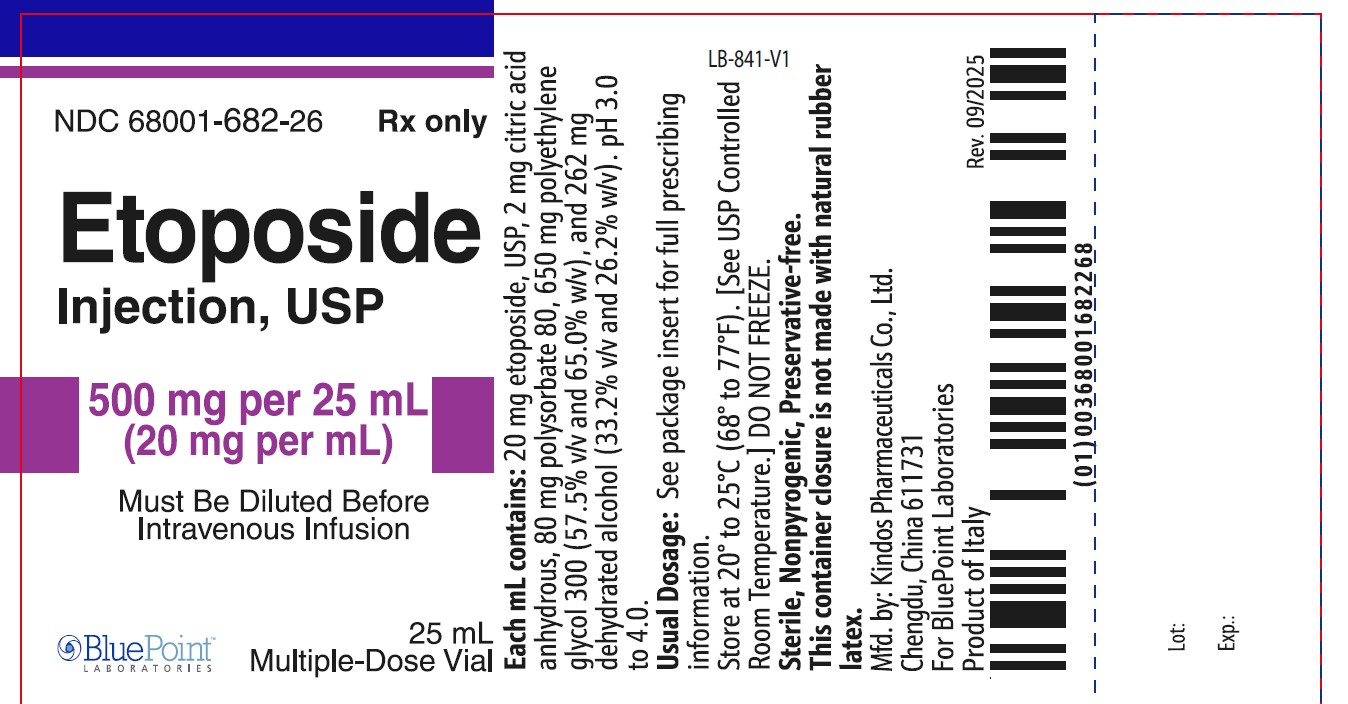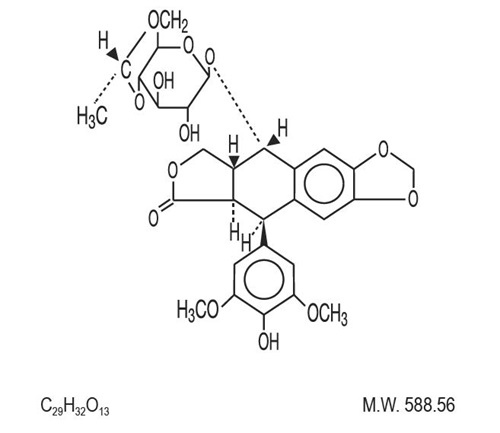 DRUG LABEL: Etoposide
NDC: 68001-681 | Form: INJECTION, SOLUTION, CONCENTRATE
Manufacturer: BluePoint Laboratories
Category: prescription | Type: HUMAN PRESCRIPTION DRUG LABEL
Date: 20251201

ACTIVE INGREDIENTS: ETOPOSIDE 20 mg/1 mL
INACTIVE INGREDIENTS: ANHYDROUS CITRIC ACID; POLYSORBATE 80; POLYETHYLENE GLYCOL 300; ALCOHOL

Etoposide Injection, USP
For Intravenous Use Only
Rx only

WARNINGS

Etoposide injection should be administered under the supervision of a qualified physician experienced in the use of cancer chemotherapeutic agents. Severe myelosuppression with resulting infection or bleeding may occur.

DESCRIPTION

Etoposide Injection, USP (also commonly known as VP-16) is a semisynthetic derivative of podophyllotoxin used in the treatment of certain neoplastic diseases. It is 4'-demethylepipodophyllotoxin 9-[4,6-0-(R)-ethylidene-β-D-glucopyranoside]. It is very soluble in methanol and chloroform, slightly soluble in ethanol, and sparingly soluble in water and ether. It is made more miscible with water by means of organic solvents.

Etoposide Injection, USP is available for intravenous use as a sterile 20 mg per mL solution in 100 mg (5 mL), 500 mg (25 mL), or 1 g (50 mL) sterile, multiple dose vials. The pH of the clear, colorless to yellow solution is 3.0 to 4.0.

Each mL contains: 20 mg etoposide, USP, 2 mg citric acid anhydrous, 80 mg polysorbate 80, 650 mg polyethylene glycol 300 (57.5% v/v and 65.0% w/v), and 262 mg dehydrated alcohol (33.2% v/v and 26.2% w/v).

The structural formula is:

CLINICAL PHARMACOLOGY

Etoposide Injection has been shown to cause metaphase arrest in chick fibroblasts. Its main effect, however, appears to be at the G2portion of the cell cycle in mammalian cells. Two different dose-dependent responses are seen. At high concentrations (10 mcg/mL or more), lysis of cells entering mitosis is observed. At low concentrations (0.3 to 10 mcg/mL), cells are inhibited from entering prophase. It does not interfere with microtubular assembly. The predominant macromolecular effect of etoposide appears to be the induction of DNA strand breaks by an interaction with DNA topoisomerase II or the formation of free radicals.

Pharmacokinetics

On intravenous administration, the disposition of etoposide is best described as a biphasic process with a distribution half-life of about 1.5 hours and terminal elimination half-life ranging from 4 to 11 hours. Total body clearance values range from 33 to 48 mL/min or 16 to 36 mL/min/m^2and, like the terminal elimination half-life, are independent of dose over a range 100 to 600 mg/m^2. Over the same dose range, the areas under the plasma concentration vs time curves (AUC) and the maximum plasma concentration (Cmax) values increase linearly with dose. Etoposide does not accumulate in the plasma following daily administration of 100 mg/m^2for 4 to 5 days.

The mean volumes of distribution at steady state fall in the range of 18 to 29 liters or 7 to 17 L/m^2. Etoposide enters the CSF poorly. Although it is detectable in CSF and intracerebral tumors, the concentrations are lower than in extracerebral tumors and in plasma. Etoposide concentrations are higher in normal lung than in lung metastases and are similar in primary tumors and normal tissues of the myometrium. In vitro, etoposide is highly protein bound (97%) to human plasma proteins. An inverse relationship between plasma albumin levels and etoposide renal clearance is found in children. In a study determining the effect of other therapeutic agents on the in vitrobinding of carbon-14 labeled etoposide to human serum proteins, only phenylbutazone, sodium salicylate, and aspirin displaced protein-bound etoposide at concentrations achieved in vivo.

Etoposide binding ratio correlates directly with serum albumin in patients with cancer and in normal volunteers. The unbound fraction of etoposide significantly correlated with bilirubin in a population of cancer patients. Data have suggested a significant inverse correlation between serum albumin concentration and free fraction of etoposide (see PRECAUTIONSsection).

After intravenous administration of^14C-etoposide (100 to 124 mg/m^2), mean recovery of radioactivity in the urine was 56% of the dose at 120 hours, 45% of which was excreted as etoposide; fecal recovery of radioactivity was 44% of the dose at 120 hours.

In children, approximately 55% of the dose is excreted in the urine as etoposide in 24 hours. The mean renal clearance of etoposide is 7 to 10 mL/min/m^2or about 35% of the total body clearance over a dose range of 80 to 600 mg/m^2. Etoposide, therefore, is cleared by both renal and nonrenal processes, i.e., metabolism and biliary excretion. The effect of renal disease on plasma etoposide clearance is not known.

Biliary excretion of unchanged drug and/or metabolites is an important route of etoposide elimination as fecal recovery of radioactivity is 44% of the intravenous dose. The hydroxy acid metabolite [4'-demethylepipodophyllic acid-9-(4,6-O-(R)-ethylidene-β-D-glucopyranoside)], formed by opening of the lactone ring, is found in the urine of adults and children. It is also present in human plasma, presumably as the transisomer. Glucuronide and/or sulfate conjugates of etoposide are also excreted in human urine. Only 8% or less of an intravenous dose is excreted in the urine as radiolabeled metabolites of^14C-etoposide. In addition, O-demethylation of the dimethoxyphenol ring occurs through the CYP450 3A4 isoenzyme pathway to produce the corresponding catechol.

After either intravenous infusion or oral capsule administration, the Cmaxand AUC values exhibit marked intra- and inter-subject variability.

In adults, the total body clearance of etoposide is correlated with creatinine clearance, serum albumin concentration, and nonrenal clearance. Patients with impaired renal function receiving etoposide have exhibited reduced total body clearance, increased AUC and a lower volume of distribution at steady state (see PRECAUTIONSsection). Use of cisplatin therapy is associated with reduced total body clearance. In children, elevated serum SGPT levels are associated with reduced drug total body clearance. Prior use of cisplatin may also result in a decrease of etoposide total body clearance in children.

Although some minor differences in pharmacokinetic parameters between age and gender have been observed, these differences were not considered clinically significant.

INDICATIONS AND USAGE

Etoposide Injection is indicated in the management of the following neoplasms:

Refractory Testicular Tumors

Etoposide Injection in combination therapy with other approved chemotherapeutic agents in patients with refractory testicular tumors who have already received appropriate surgical, chemotherapeutic, and radiotherapeutic therapy.

Small Cell Lung Cancer

Etoposide Injection and/or capsules in combination with other approved chemotherapeutic agents as first line treatment in patients with small cell lung cancer.

CONTRAINDICATIONS

Etoposide injection is contraindicated in patients who have demonstrated a previous hypersensitivity to etoposide or any component of the formulation.

WARNINGS

Patients being treated with etoposide injection must be frequently observed for myelosuppression both during and after therapy. Myelosuppression resulting in death has been reported. Dose-limiting bone marrow suppression is the most significant toxicity associated with etoposide injection therapy. Therefore, the following studies should be obtained at the start of therapy and prior to each subsequent cycle of etoposide injection: platelet count, hemoglobin, white blood cell count, and differential. The occurrence of a platelet count below 50,000/mm^3or an absolute neutrophil count below 500/mm^3is an indication to withhold further therapy until the blood counts have sufficiently recovered.

Physicians should be aware of the possible occurrence of an anaphylactic reaction manifested by chills, fever, tachycardia, bronchospasm, dyspnea, and hypotension. Higher rates of anaphylactic-like reactions have been reported in children who received infusions at concentrations higher than those recommended. The role that concentration of infusion (or rate of infusion) plays in the development of anaphylactic-like reactions is uncertain (see ADVERSE REACTIONSsection). Treatment is symptomatic. The infusion should be terminated immediately, followed by the administration of pressor agents, corticosteroids, antihistamines, or volume expanders at the discretion of the physician.

For parenteral administration, etoposide injection should be given only by slow intravenous infusion (usually over a 30- to 60-minute period) since hypotension has been reported as a possible side effect of rapid intravenous injection.

Pregnancy

Etoposide Injection can cause fetal harm when administered to a pregnant woman. Etoposide has been shown to be teratogenic in mice and rats.

In rats, an intravenous etoposide dose of 0.4 mg/kg/day (about 1/20thof the human dose on a mg/m^2basis) during organogenesis caused maternal toxicity, embryotoxicity, and teratogenicity (skeletal abnormalities, exencephaly, encephalocele, and anophthalmia); higher doses of 1.2 and 3.6 mg/kg/day (about 1/7thand 1/2 of human dose on a mg/m^2basis) resulted in 90 and 100% embryonic resorptions. In mice, a single 1 mg/kg (1/16thof human dose on a mg/m^2basis) dose of etoposide administered intraperitoneally on days 6, 7, or 8 of gestation caused embryotoxicity, cranial abnormalities, and major skeletal malformations. An I.P. dose of 1.5 mg/kg (about 1/10thof human dose on a mg/m^2basis) on day 7 of gestation caused an increase in the incidence of intrauterine death and fetal malformations and a significant decrease in the average fetal body weight.

Women of childbearing potential should be advised to avoid becoming pregnant. If this drug is used during pregnancy, or if the patient becomes pregnant while receiving this drug, the patient should be warned of the potential hazard to the fetus.

Etoposide injection should be considered a potential carcinogen in humans. The occurrence of acute leukemia with or without a preleukemic phase has been reported in rare instances in patients treated with etoposide alone or in association with other neoplastic agents. The risk of development of a preleukemic or leukemic syndrome is unclear. Carcinogenicity tests with etoposide injection have not been conducted in laboratory animals.

PRECAUTIONS

General

In all instances where the use of etoposide injection is considered for chemotherapy, the physician must evaluate the need and usefulness of the drug against the risk of adverse reactions. Most such adverse reactions are reversible if detected early. If severe reactions occur, the drug should be reduced in dosage or discontinued and appropriate corrective measures should be taken according to the clinical judgment of the physician. Reinstitution of etoposide injection therapy should be carried out with caution, and with adequate consideration of the further need for the drug and alertness as to possible recurrence of toxicity.

Patients with low serum albumin may be at an increased risk for etoposide associated toxicities.

Drug Interactions

High-dose cyclosporin A resulting in concentrations above 2000 ng/mL administered with oral etoposide has led to an 80% increase in etoposide exposure with a 38% decrease in total body clearance of etoposide compared to etoposide alone.

Laboratory Tests

Periodic complete blood counts should be done during the course of etoposide injection treatment. They should be performed prior to each cycle of therapy and at appropriate intervals during and after therapy. At least one determination should be done prior to each dose of etoposide injection.

Renal Impairment

In patients with impaired renal function, the following initial dose modification should be considered based on measured creatinine clearance:

Measured Creatinine Clearance | >50 mL/min | 15 to 50 mL/min
etoposide | 100% of dose | 75% of dose

Subsequent etoposide injection dosing should be based on patient tolerance and clinical effect.

Data are not available in patients with creatinine clearances <15 mL/min and further dose reduction should be considered in these patients.

Carcinogenesis, Mutagenesis, Impairment of Fertility (see WARNINGS section)

Etoposide has been shown to be mutagenic in Ames assay.

Treatment of Swiss-Albino mice with 1.5 mg/kg I.P. of etoposide injection on day 7 of gestation increased the incidence of intrauterine death and fetal malformations as well as significantly decreased the average fetal body weight. Maternal weight gain was not affected.

Irreversible testicular atrophy was present in rats treated with etoposide intravenously for 30 days at 0.5 mg/kg/day (about 1/16thof the human dose on a mg/m^2basis).

Pregnancy

Teratogenic Effects

Pregnancy "Category D."

(See WARNINGSsection.)

Nursing Mothers

It is not known whether this drug is excreted in human milk. Because many drugs are excreted in human milk and because of the potential for serious adverse reactions in nursing infants from etoposide injection, a decision should be made whether to discontinue nursing or to discontinue the drug, taking into account the importance of the drug to the mother.

Pediatric Use

Safety and effectiveness in pediatric patients have not been established.

Etoposide injection contains polysorbate 80. In premature infants, a life-threatening syndrome consisting of liver and renal failure, pulmonary deterioration, thrombocytopenia, and ascites has been associated with an injectable vitamin E product containing polysorbate 80. Anaphylactic reactions have been reported in pediatric patients (see WARNINGSsection).

Geriatric Use

Clinical studies of etoposide injection for the treatment of refractory testicular tumors did not include sufficient numbers of patients aged 65 years and over to determine whether they respond differently from younger patients. Of more than 600 patients in four clinical studies in the NDA databases who received etoposide injection or etoposide phosphate in combination with other chemotherapeutic agents for the treatment of small cell lung cancer (SCLC), about one third were older than 65 years. When advanced age was determined to be a prognostic factor for response or survival in these studies, comparisons between treatment groups were performed for the elderly subset. In the one study (etoposide in combination with cyclophosphamide and vincristine compared with cyclophosphamide and vincristine or cyclophosphamide, vincristine, and doxorubicin) where age was a significant prognostic factor for survival, a survival benefit for elderly patients was observed for the etoposide regimen compared with the control regimens. No differences in myelosuppression were seen between elderly and younger patients in these studies except for an increased frequency of WHO Grade III or IV leukopenia among elderly patients in a study of etoposide phosphate or etoposide in combination with cisplatin. Elderly patients in this study also had more anorexia, mucositis, dehydration, somnolence, and elevated BUN levels than younger patients.

In five single-agent studies of etoposide phosphate in patients with a variety of tumor types, 34% of patients were age 65 years or more. WHO Grade III or IV leukopenia, granulocytopenia, and asthenia were more frequent among elderly patients.

Postmarketing experience also suggests that elderly patients may be more sensitive to some of the known adverse effects of etoposide, including myelosuppression, gastrointestinal effects, infectious complications, and alopecia.

Although some minor differences in pharmacokinetic parameters between elderly and nonelderly patients have been observed, these differences were not considered clinically significant.

Etoposide and its metabolites are known to be substantially excreted by the kidney, and the risk of adverse reactions to this drug may be greater in patients with impaired renal function. Because elderly patients are more likely to have decreased renal function, care should be taken in dose selection, and it may be useful to monitor renal function (see PRECAUTIONS, Renal Impairmentfor recommended dosing adjustments in patients with renal impairment).

ADVERSE REACTIONS

The following data on adverse reactions are based on both oral and intravenous administration of etoposide injection as a single agent, using several different dose schedules for treatment of a wide variety of malignancies.

Hematologic Toxicity

Myelosuppression is dose related and dose limiting, with granulocyte nadirs occurring 7 to 14 days after drug administration and platelet nadirs occurring 9 to 16 days after drug administration. Bone marrow recovery is usually complete by day 20, and no cumulative toxicity has been reported. Fever and infection have also been reported in patients with neutropenia. Death associated with myelosuppression has been reported.

The occurrence of acute leukemia with or without a preleukemic phase has been reported rarely in patients treated with etoposide injection in association with other antineoplastic agents (see WARNINGSsection).

Gastrointestinal Toxicity

Nausea and vomiting are the major gastrointestinal toxicities. The severity of such nausea and vomiting is generally mild to moderate with treatment discontinuation required in 1% of patients. Nausea and vomiting can usually be controlled with standard antiemetic therapy. Mild to severe mucositis/esophagitis may occur. Gastrointestinal toxicities are slightly more frequent after oral administration than after intravenous infusion.

Hypotension

Transient hypotension following rapid intravenous administration has been reported in 1% to 2% of patients. It has not been associated with cardiac toxicity or electrocardiographic changes. No delayed hypotension has been noted. To prevent this rare occurrence, it is recommended that etoposide injection be administered by slow intravenous infusion over a 30- to 60-minute period. If hypotension occurs, it usually responds to cessation of the infusion and administration of fluids or other supportive therapy as appropriate. When restarting the infusion, a slower administration rate should be used.

Allergic Reactions

Anaphylactic-like reactions characterized by chills, fever, tachycardia, bronchospasm, dyspnea, and/or hypotension have been reported to occur in 0.7% to 2% of patients receiving intravenous etoposide injection and in less than 1% of the patients treated with the oral capsules. These reactions have usually responded promptly to the cessation of the infusion and administration of pressor agents, corticosteroids, antihistamines, or volume expanders as appropriate; however, the reactions can be fatal. Hypertension and/or flushing have also been reported. Blood pressure usually normalizes within a few hours after cessation of the infusion. Anaphylactic-like reactions have occurred during the initial infusion of etoposide injection.

Facial/tongue swelling, coughing, diaphoresis, cyanosis, tightness in throat, laryngospasm, back pain, and/or loss of consciousness have sometimes occurred in association with the above reactions. In addition, an apparent hypersensitivity-associated apnea has been reported rarely.

Rash, urticaria, and/or pruritus have infrequently been reported at recommended doses. At investigational doses, a generalized pruritic erythematous maculopapular rash, consistent with perivasculitis, has been reported.

Alopecia

Reversible alopecia, sometimes progressing to total baldness, was observed in up to 66% of patients.

Other Toxicities

The following adverse reactions have been infrequently reported: abdominal pain, aftertaste, constipation, dysphagia, asthenia, fatigue, malaise, somnolence, transient cortical blindness, optic neuritis, interstitial pneumonitis/pulmonary fibrosis, fever, seizure (occasionally associated with allergic reactions), Stevens-Johnson syndrome, and toxic epidermal necrolysis, pigmentation, and a single report of radiation recall dermatitis.

Hepatic toxicity, generally in patients receiving higher doses of the drug than those recommended, has been reported with etoposide injection. Metabolic acidosis has also been reported in patients receiving higher doses.

Reports of extravasation with swelling have been received postmarketing. Rarely extravasation has been associated with necrosis and venous induration.

The incidences of adverse reactions in the table that follows are derived from multiple data bases from studies in 2,081 patients when etoposide injection was used either orally or by injection as a single agent.

ADVERSE DRUG EFFECT | PERCENT RANGE OF REPORTED INCIDENCE
Hematologic toxicity
Leukopenia (less than 1,000 WBC/mm^3) | 3 to 17
Leukopenia (less than 4,000 WBC/mm^3) | 60 to 91
Thrombocytopenia (less than 50,000 platelets/mm^3) | 1 to 20
Thrombocytopenia (less than 100,000; platelets/mm^3) | 22 to 41
Anemia | 0 to 33
Gastrointestinal toxicity
Nausea and vomiting | 31 to 43
Abdominal pain | 0 to 2
Anorexia | 10 to 13
Diarrhea | 1 to 13
Stomatitis | 1 to 6
Hepatic | 0 to 3
Alopecia | 8 to 66
Peripheral neurotoxicity | 1 to 2
Hypotension | 1 to 2
Allergic reaction | 1 to 2

To report SUSPECTED ADVERSE REACTIONS, contact Meitheal Pharmaceuticals, Inc. at 1-844-824-8426 or FDA at 1-800-FDA-1088 or www.fda.gov/medwatch.

OVERDOSAGE

No proven antidotes have been established for etoposide injection overdosage.

DOSAGE AND ADMINISTRATION

Note: Plastic devices made of acrylic or ABS (a polymer composed of acrylonitrile, butadiene, and styrene) have been reported to crack and leak when used with undiluted etoposide injection.

Etoposide Injection

The usual dose of etoposide injection in testicular cancer in combination with other approved chemotherapeutic agents ranges from 50 to 100 mg/m^2/day on days 1 through 5 to 100 mg/m^2/day on days 1, 3, and 5.

In small cell lung cancer, the etoposide injection dose in combination with other approved chemotherapeutic drugs ranges from 35 mg/m^2/day for 4 days to 50 mg/m^2/day for 5 days.

For recommended dosing adjustments in patients with renal impairment see PRECAUTIONSsection.

Chemotherapy courses are repeated at 3- to 4-week intervals after adequate recovery from any toxicity.

The dosage should be modified to take into account the myelosuppressive effects of other drugs in the combination or the effects of prior x-ray therapy or chemotherapy which may have compromised bone marrow reserve.

Administration Precautions

As with other potentially toxic compounds, caution should be exercised in handling and preparing the solution of etoposide injection. Skin reactions associated with accidental exposure to etoposide injection may occur. The use of gloves is recommended. If etoposide injection solution contacts the skin or mucosa, immediately and thoroughly wash the skin with soap and water and flush the mucosa with water.

Preparation for Intravenous Administration

Etoposide injection must be diluted prior to use with either 5% Dextrose Injection, USP, or 0.9% Sodium Chloride Injection, USP, to give a final concentration of 0.2 to 0.4 mg/mL. If solutions are prepared at concentrations above 0.4 mg/mL, precipitation may occur. Hypotension following rapid intravenous administration has been reported, hence, it is recommended that the etoposide injection solution be administered over a 30- to 60-minute period. A longer duration of administration may be used if the volume of fluid to be infused is a concern. Etoposide injection should not be given by rapid intravenous injection.

Parenteral drug products should be inspected visually for particulate matter and discoloration (see DESCRIPTIONsection) prior to administration whenever solution and container permit.

Stability

Unopened vials of etoposide injection are stable until the date indicated on the package at room temperature (25°C). Vials diluted as recommended to a concentration of 0.2 to 0.4 mg/mL are stable for 96 and 24 hours, respectively, at room temperature (25°C) under normal room fluorescent light in both glass and plastic containers.

Procedures for proper handling and disposalof anticancer drugs should be considered. Several guidelines on this subject have been published.^1-8There is no general agreement that all of the procedures recommended in the guidelines are necessary or appropriate.

HOW SUPPLIED

Etoposide Injection, USP, 20 mg per mL is supplied as follows:

NDC | Etoposide Injection, USP (20 mg per mL) | Package Factor
68001- 681-25 | 100 mg per 5 mL Multi-Dose Vial | 1 vial per carton
68001- 682-26 | 500 mg per 25 mL Multi-Dose Vial | 1 vial per carton
68001- 683-27 | 1 gram per 50 mL Multi-Dose Vial | 1 vial per carton

All are available individually packaged.

Store at 20° to 25°C (68° to 77°F). [See USP Controlled Room Temperature.]

DO NOT FREEZE.

Sterile, Nonpyrogenic, Preservative-free.
The container closure is not made with natural rubber latex.

REFERENCES

1. ONS Clinical Practice Committee. Cancer Chemotherapy Guidelines and Recommendations for Practice Pittsburgh, PA: Oncology Nursing Society; 1999:32-41.

2. Recommendations for the safe handling of parenteral antineoplastic drugs. Washington, DC: Division of Safety, National Institutes of Health; 1983. US Dept of Health and Human Services, Public Health Service publication NIH 83-2621.

3. AMA Council on Scientific Affairs. Guidelines for handling parenteral antineoplastics. JAMA. 1985;253:1590-1591.

4. National Study Commission on Cytotoxic Exposure. Recommendations for handling cytotoxic agents. 1987. Available from Louis P. Jeffrey, Chairman, National Study Commission on Cytotoxic Exposure. Massachusetts College of Pharmacy and Allied Health Sciences, 179 Longwood Avenue, Boston, MA 02115.

5. Clinical Oncological Society of Australia. Guidelines and recommendations for safe handling of antineoplastic agents. Med J Australia. 1983;1:426-428.

6. Jones RB, Frank R, Mass T. Safe handling of chemotherapeutic agents: a report from the Mount Sinai Medical Center. CA-A Cancer J for Clin. 1983;33:258-263.

7. American Society of Hospital Pharmacists. ASHP technical assistance bulletin on handling cytotoxic and hazardous drugs. Am J Hosp Pharm. 1990;47:1033-1049.

8. Controlling Occupational Exposure to Hazardous Drugs. (OSHA Work-Practice Guidelines.). Am J Health-SystPharm. 1996;53:1669-1685.

Manufactured By:

Kindos Pharmaceuticals Co., Ltd.
Chengdu, China 611731

For BluePoint Laboratories

Product of Italy

Rev.: 09/2025

PACKAGE LABEL PRINCIPAL DISPLAY PANEL - Etoposide Injection, USP 100 mg per 5 mL Vial Label

NDC 68001-681-25

Rx Only

Etoposide Injection, USP

100 mg per 5 mL

(20 mg per mL)

Must Be Diluted Before Intravenous Infusion

5 mL Multiple-Dose Vial

PACKAGE LABEL PRINCIPAL DISPLAY PANEL - Etoposide Injection, USP 100 mg per 5 mL Carton

NDC 68001-681-25

Rx Only

Etoposide Injection, USP

100 mg per 5 mL

(20 mg per mL)

Warning: Cytotoxic Agent

Must Be Diluted Before

Intravenous Infusion

1 x 5 mL Multiple-Dose Vial

PACKAGE LABEL PRINCIPAL DISPLAY PANEL - Etoposide Injection, USP 500 mg per 25 mL Vial Label

NDC 68001-682-26

Rx Only

Etoposide Injection, USP

500 mg per 25 mL

(20 mg per mL)

Must Be Diluted Before

Intravenous Infusion

25 mL Multiple-Dose Vial

PACKAGE LABEL PRINCIPAL DISPLAY PANEL - Etoposide Injection, USP 500 mg per 25 mL Carton

NDC 68001-682-26

Rx Only

Etoposide Injection, USP

500 mg per 25 mL

(20 mg per mL)

Warning: Cytotoxic Agent

Must Be Diluted Before

Intravenous Infusion

1 x 25 mL Multiple-Dose Vial

PACKAGE LABEL PRINCIPAL DISPLAY PANEL - Etoposide Injection, USP 1 gram per 50 mL Vial Label

NDC 68001-683-27

Rx Only

Etoposide Injection, USP

1 gram per 50 mL

(20 mg per mL)

Must Be Diluted Before Intravenous Infusion

50 mL Multiple-Dose Vial

PACKAGE LABEL PRINCIPAL DISPLAY PANEL - Etoposide Injection, USP 1 gram per 50 mL Carton Label

NDC 68001-683-27

Rx Only

Etoposide Injection, USP

1 gram per 50 mL

(20 mg per mL)

Warning: Cytotoxic Agent

Must Be Diluted Before Intravenous Infusion

1 x 50 mL Multiple-Dose Vial